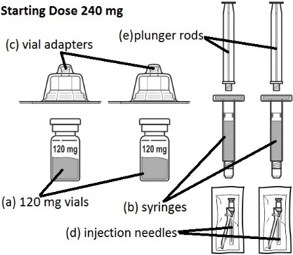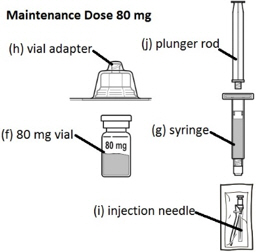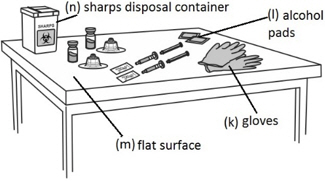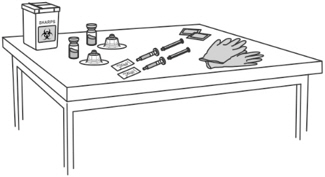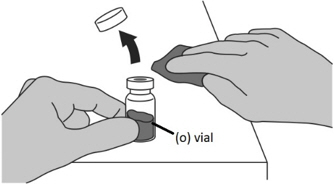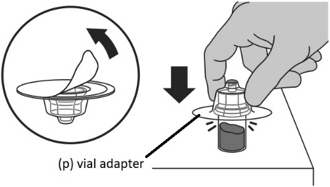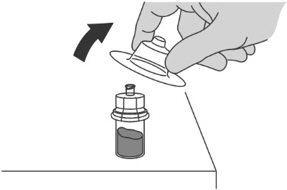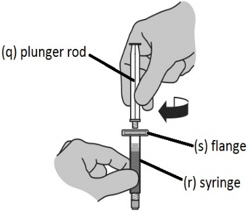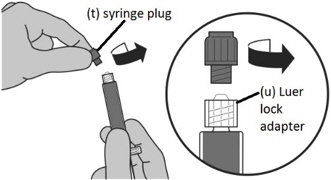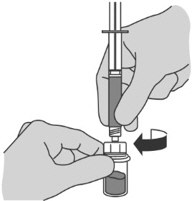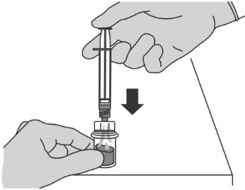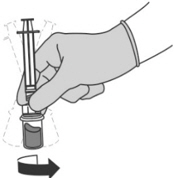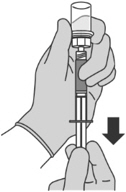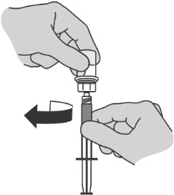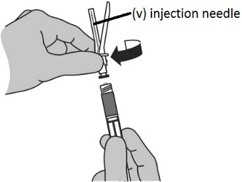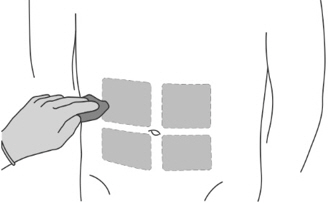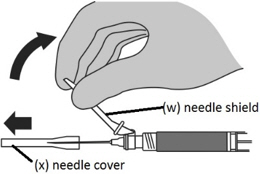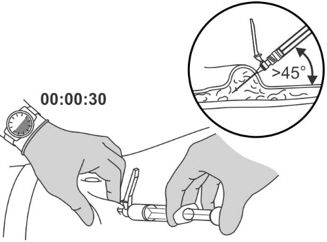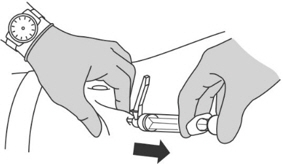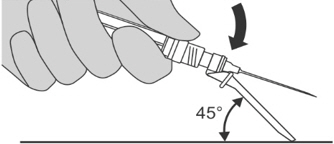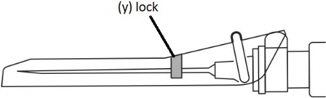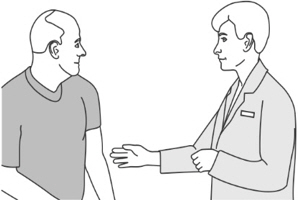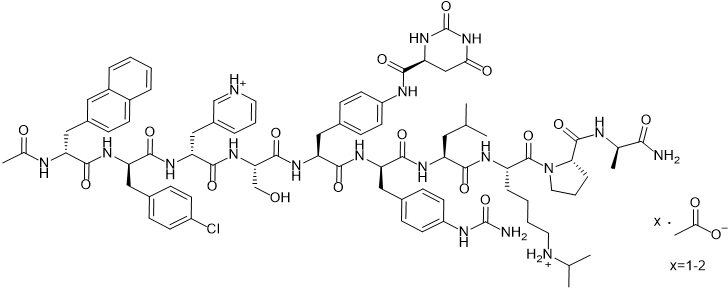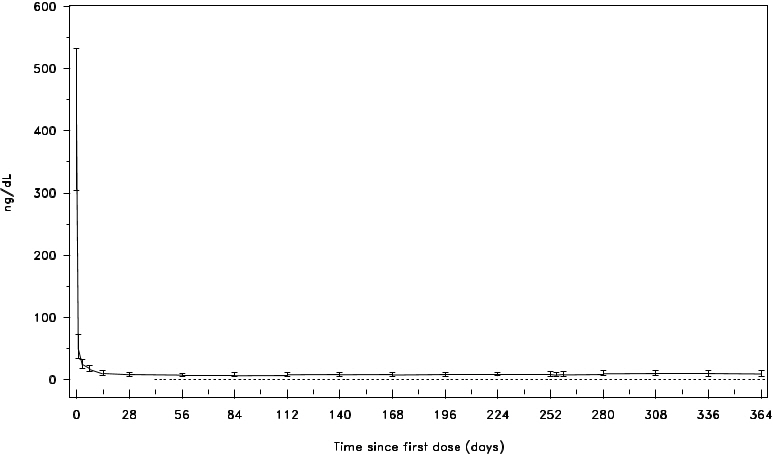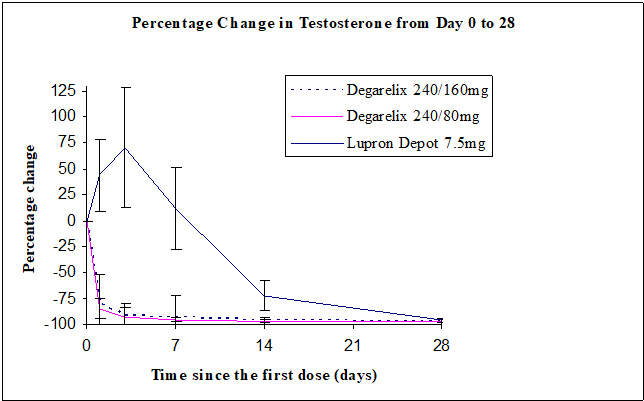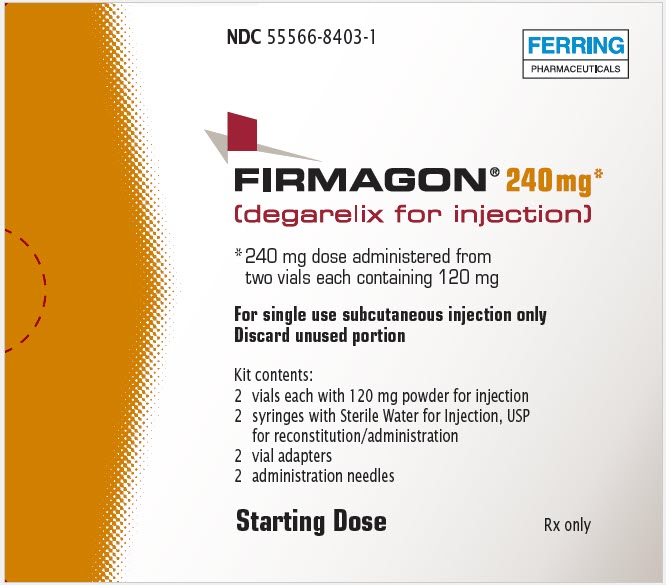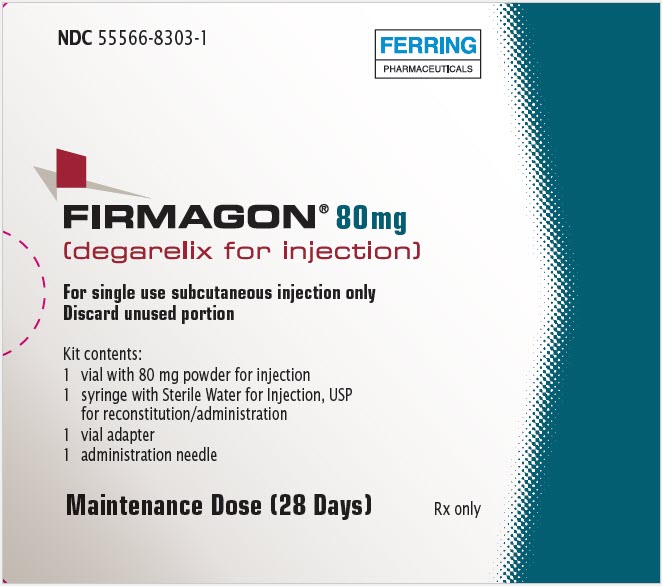 DRUG LABEL: FIRMAGON
NDC: 55566-8403 | Form: KIT | Route: SUBCUTANEOUS
Manufacturer: Ferring Pharmaceuticals Inc.
Category: prescription | Type: HUMAN PRESCRIPTION DRUG LABEL
Date: 20240130

ACTIVE INGREDIENTS: DEGARELIX 40 mg/1 mL
INACTIVE INGREDIENTS: MANNITOL 50 mg/1 mL; WATER

HIGHLIGHTS OF PRESCRIBING INFORMATION

These highlights do not include all the information needed to use FIRMAGON safely and effectively. See full prescribing information for FIRMAGON.
FIRMAGON® (degarelix for injection) for subcutaneous use
Initial U.S. Approval: 2008

RECENT MAJOR CHANGES

Warnings and Precautions, Embryo-Fetal Toxicity (5.4) | 02/2020

1 INDICATIONS AND USAGE

FIRMAGON is a GnRH receptor antagonist indicated for treatment of patients with advanced prostate cancer. (1)

2 DOSAGE AND ADMINISTRATION

- FIRMAGON is for subcutaneous use only
- Starting Dosage: 240 mg given as two injections of 120 mg each (2.1)
- Maintenance Dosage: 80 mg administered as a single injection every 28 days (2.1)

3 DOSAGE FORMS AND STRENGTHS

For injection:

- FIRMAGON (240 mg): Two single-dose vials each delivering 120 mg of degarelix in a lyophilized powder for reconstitution supplied with diluent in two prefilled syringes (3)
- FIRMAGON (80 mg): One single-dose vial delivering 80 mg of degarelix in a lyophilized powder for reconstitution supplied with diluent in one prefilled syringe (3)

4 CONTRAINDICATIONS

- Patients with history of severe hypersensitivity reactions to degarelix or to any of the product components (4)

5 WARNINGS AND PRECAUTIONS

- Hypersensitivity: Anaphylaxis, urticaria and angioedema have been reported. Discontinue FIRMAGON if a severe hypersensitivity reaction occurs and manage as clinically indicated (5.1)
- QT Interval Prolongation: Androgen deprivation therapy treatment with FIRMAGON may prolong the QT interval. (5.2)
- Embryo-Fetal Toxicity: FIRMAGON can cause fetal harm. (5.4, 8.1)

6 ADVERSE REACTIONS

Most common adverse reactions (≥10%) are injection site reactions (e.g., pain, erythema, swelling or induration), hot flashes, and increases in serum levels of transaminases and gamma-glutamyltransferase (GGT) (6.1)

To report SUSPECTED ADVERSE REACTIONS, contact Ferring at 1-888-FERRING (1-888-337-7464) or FDA at 1-800-FDA-1088 or www.fda.gov/medwatch.

8 USE IN SPECIFIC POPULATIONS

- Females and males of reproductive potential: FIRMAGON may impair fertility (8.3)
- Patients with severe liver or kidney dysfunction have not been studied and caution is therefore warranted (8)

FULL PRESCRIBING INFORMATION

1 INDICATIONS AND USAGE

FIRMAGON® is indicated for treatment of patients with advanced prostate cancer.

2 DOSAGE AND ADMINISTRATION

2.1 Dosing information

FIRMAGON is administered as a subcutaneous injection in the abdominal region only at the dosages in Table 1 below.

Table 1: FIRMAGON Recommended Dosages
Starting Dosage | Maintenance Dosage – Administered once every 28 days
- 240 mg given as two subcutaneous injections of 120 mg at a concentration of 40 mg/mL | - The first maintenance dose should be given 28 days after the starting dose. - 80 mg given as one subcutaneous injection at a concentration of 20 mg/mL

2.2 Reconstitution and Administration Instructions

FIRMAGON is to be administered by a healthcare professional only.

Before administering FIRMAGON read the Instructions for reconstitution and administration carefully.

As with other drugs administered by subcutaneous injection, the injection site should vary periodically. Injections should be given only in areas of the abdomen that will not be exposed to pressure, e.g., not close to waistband or belt nor close to the ribs.

FIRMAGON is supplied as a powder to be reconstituted with Sterile Water for Injection, USP.

- Starting dose (240 mg): Two single-dose vials each delivering 120 mg of degarelix in a white to off-white lyophilized powder for reconstitution supplied with diluent in two prefilled syringes. Each vial is to be reconstituted with a prefilled syringe containing 3 mL of Sterile Water for Injection. 3 mL is withdrawn to deliver 120 mg degarelix at a concentration of 40 mg/mL.
- Maintenance dose (80 mg): One single-dose vial delivering 80 mg of degarelix in a white to off-white lyophilized powder for reconstitution supplied with diluent in one prefilled syringe. Each vial is to be reconstituted with a prefilled syringe containing 4.2 mL of Sterile Water for Injection. 4 mL is withdrawn to deliver 80 mg degarelix at a concentration of 20 mg/mL.

Follow the instructions for reconstitution closely and read the complete instructions before performing the subcutaneous injection.

Reconstituted drug must be administered within one hour after addition of Sterile Water for Injection, USP.

Do not shake the vials.

Follow aseptic technique.

FIRMAGON 240 mg Starting Dose Kit contains:

- 2 vials containing the 120 mg FIRMAGON powder (a)
- 2 syringes containing Sterile Water for Injection, USP (b)
- 2 vial adapters (c)
- 2 25 gauge × 1 inch injection needles (d)
- 2 plunger rods (e)

FIRMAGON 80 mg Maintenance Dose Kit contains:

- 1 vial containing the 80 mg FIRMAGON powder (f)
- 1 syringe containing Sterile Water for Injection, USP (g)
- 1 vial adapter (h)
- 1 25 gauge × 1 inch injection needle (i)
- 1 plunger rod (j)

In addition the healthcare professional will need:

- gloves (k)
- alcohol pads (l)
- a clean, flat surface (m) to work on, like a table
- a sharps disposal container (n) for throwing away your used needles and syringes. See "Disposing used needles and syringes" at the end of these instructions.

The drug product must be prepared using the following instructions:

NOTE: The mixing process must be repeated for the two injections of the Starting Dose prior to injecting the product into the patient's abdomen.

Step 1: Attaching the vial adaptor to the vial

- Thoroughly wash your hands using soap and water and put on a pair of clean gloves.
- Place all the supplies required on a clean surface.
- Check that there is powder in the FIRMAGON vial and that the Sterile Water for Injection, USP is clear and free from particles.

IMPORTANT: DO NOT USE if there is no powder in the vial or the Sterile Water for Injection, USP is discolored.

- Uncap the vial containing the FIRMAGON powder (o).
- Wipe the vial rubber stopper with an alcohol pad.

IMPORTANT: Do not touch the top of the vial after wiping.

- Peel off the seal from the vial adaptor cover.

IMPORTANT: Do not touch the vial adapter.

- Firmly press the vial adaptor (p) onto the vial containing the FIRMAGON powder until the adaptor snaps into place.

- Pull the vial adaptor cover off the vial.

Step 2: Assembling the syringe

- Insert the plunger rod (q) into the prefilled syringe containing Sterile Water for Injection, USP (r) and screw the plunger rod clockwise to tighten.

IMPORTANT: Do not pull the back stopper (flange) (s) off the syringe.
NOTE: You will only feel light resistance screwing the plunger rod in position.

Step 3: Transferring Sterile Water for Injection, USP from the syringe to the vial

- Unscrew the gray syringe plug (t) attached to the Luer lock adaptor on the syringe.

IMPORTANT: Do not pull off the Luer lock adaptor (u).

- Carefully twist the prefilled syringe containing Sterile Water for Injection, USP onto the vial adapter on the FIRMAGON powder vial, until it is tight.

IMPORTANT: Be careful not to over twist the syringe.

- Press the plunger slowly to transfer all the Sterile Water for Injection, USP from the syringe to the FIRMAGON powder vial.

Step 4: Preparing the reconstituted injection

- With the syringe still attached to the vial adaptor, swirl gently until the liquid is clear with no powder or visible particles.

IMPORTANT:

- Do not shake the vial as this will cause bubbles.
- Reconstitute just prior to administration.

NOTE: If the powder adheres to the side of the vial, tilt the vial slightly. A ring of small air bubbles on the surface of the liquid is acceptable.
Reconstitution time can take up to 15 min but usually takes a few minutes.

Step 5: Transferring the liquid to the syringe

- Turn the vial completely upside down and pull down the plunger to withdraw all of the reconstituted liquid from the vial to the syringe.
- Tap the syringe gently with your fingers to raise air bubbles in the syringe tip.
- Press the plunger to the line marked on the syringe to expel all air bubbles.

Step 6: Preparing the syringe for injection

- Holding the vial adaptor detach the syringe from the vial by unscrewing the syringe from the vial adaptor.

NOTE: Reconstitute just prior to administration.

- While holding the syringe with the tip pointing up, screw the injection needle (v) clockwise (right) onto the syringe.

Step 7: Preparing the patient

- Select one of the four available injection sites on the abdomen.

IMPORTANT:

- Do not inject in areas where the patient will be exposed to pressure, such as area around the belt of the waistband or close to the ribs.
- Vary the injection site periodically during treatment to minimize discomfort to the patient.

- Clean the injection site with an alcohol pad.

Step 8: Performing the injection

- Move the needle shield (w) away from the needle and carefully remove the needle cover (x).

- Pinch and elevate the skin of the abdomen.
- Insert the needle into the skin at a 45 degree angle all the way to the hub.
- Do not inject into a vein or muscle. Gently pull back the plunger to check if blood is aspirated.

IMPORTANT: If blood appears in the syringe, the product should not be injected. Discontinue the injection and discard the syringe and the needle (reconstitute a new dose for the patient).

- Perform a slow, deep subcutaneous injection over 30 seconds.

- Remove the needle and then release the skin.

IMPORTANT: Do not rub the injection site after retracting the needle.

Step 9: Locking the needle into the shield

- Position the needle shield approximately 45 degrees to a flat surface.
- Press down with a firm, quick motion until a distinct, audible "click" is heard.

- Visually confirm that the needle is fully engaged under the lock (y).

IMPORTANT: Syringe is for single use only. Do not reuse the syringe and needle.

Step 10: Advising the patient

- Instruct the patient not to rub or scratch the injection site.
- Inform that some patients may feel a lump at the injection site and experience redness, soreness and discomfort for a few days after the injection.

Disposing used needles and syringes

- Put used alcohol swabs, needles and syringes in an FDA-cleared sharps disposal container right away after use. Do not throw away loose needles and syringes in the trash.
- For more information about safe sharps disposal, go to the FDA's website at: http://www.fda.gov/safesharpsdisposal.

3 DOSAGE FORMS AND STRENGTHS

For injection:

- FIRMAGON (240 mg): Two single-dose vials each delivering 120 mg of degarelix in a white to off-white lyophilized powder for reconstitution supplied with diluent in two prefilled syringes.
- FIRMAGON (80 mg): One single-dose vial delivering 80 mg of degarelix in a white to off-white lyophilized powder for reconstitution supplied with diluent in one prefilled syringe.

4 CONTRAINDICATIONS

FIRMAGON is contraindicated in patients with history of severe hypersensitivity to degarelix or to any of the product components [see Warnings and Precautions (5.1)].

5 WARNINGS AND PRECAUTIONS

5.1 Hypersensitivity Reactions

FIRMAGON is contraindicated in patients with history of severe hypersensitivity to degarelix or to any of the product components [see Contraindications (4)].

Hypersensitivity reactions, including anaphylaxis, urticaria and angioedema, have been reported post-marketing with FIRMAGON.

In case of a severe hypersensitivity reaction, discontinue FIRMAGON immediately if the injection has not been completed, and manage as clinically indicated. Patients with a known history of severe hypersensitivity reactions to FIRMAGON should not be re-challenged with FIRMAGON.

5.2 QT Interval Prolongation

Androgen deprivation therapy may prolong the QT interval. Providers should consider whether the benefits of androgen deprivation therapy outweigh the potential risks in patients with congenital long QT syndrome, congestive heart failure, frequent electrolyte abnormalities, and in patients taking drugs known to prolong the QT interval. Electrolyte abnormalities should be corrected. Consider periodic monitoring of electrocardiograms and electrolytes.

In the randomized, active-controlled trial comparing FIRMAGON to leuprolide, periodic electro-cardiograms were performed. Seven patients, three (<1%) in the pooled degarelix group and four (2%) patients in the leuprolide 7.5 mg group, had a QTcF ≥ 500 msec. From baseline to end of study, the median change for FIRMAGON was 12.3 msec and for leuprolide was 16.7 msec.

5.3 Laboratory Testing

FIRMAGON results in suppression of the pituitary gonadal system. Results of diagnostic tests of the pituitary gonadotropic and gonadal functions conducted during and after FIRMAGON may be affected. The therapeutic effect of FIRMAGON should be monitored by measuring serum concentrations of prostate-specific antigen (PSA) periodically. If PSA increases, serum concentrations of testosterone should be measured.

5.4 Embryo-Fetal Toxicity

Based on findings in animal studies, FIRMAGON can cause fetal harm and loss of pregnancy when administered to a pregnant woman. In animal developmental and reproductive toxicity studies in rats and rabbits, oral administration of degarelix during organogenesis caused embryo-fetal lethality and abortion as well as increased post-implantation loss and decreased the number of live fetuses in animals at doses less than the clinical loading dose based on body surface area. Advise pregnant patients and females of reproductive potential of the potential risk to the fetus [see Use in Specific Populations (8.1)].

6 ADVERSE REACTIONS

6.1 Clinical Trials Experience

Because clinical trials are conducted under widely varying conditions, adverse reaction rates observed in the clinical trials of a drug cannot be directly compared to rates in the clinical trials of another drug and may not reflect the rates observed in practice.

FIRMAGON was studied in a randomized, open-label trial in which patients with prostate cancer were randomized to receive FIRMAGON (subcutaneous) or leuprolide (intramuscular) monthly for 12 months [see Clinical Studies (14)].

The most common adverse reactions (≥10%) during FIRMAGON therapy are injection site reactions (e.g., pain, erythema, swelling or induration), hot flashes, and increases in serum levels of transaminases and gamma-glutamyltransferase (GGT). The majority of the adverse reactions were Grade 1 or 2, with Grade 3/4 adverse reaction incidences of 1% or less.

Adverse reactions reported in ≥ 5% of patients treated with FIRMAGON (subcutaneous) 240 mg starting dose and then 80 mg maintenance dose once every 28 days or who were treated with 7.5 mg of leuprolide (intramuscular) every 28 days are shown in Table 2.

Table 2: Adverse Reactions Reported in ≥ 5% of Patients
 | FIRMAGON 240/80 mg (subcutaneous) N = 207 | Leuprolide 7.5 mg (intramuscular) N = 201
Any adverse reaction | 79% | 78%
Body as a whole
Injection site reactions [Includes pain, erythema, swelling, induration, or nodule.] | 35% | <1%
Weight increase | 9% | 12%
Chills | 5% | 0%
Cardiovascular system
Hot flash | 26% | 21%
Hypertension | 6% | 4%
Digestive system
Increases in Transaminases and GGT | 10% | 5%
Constipation | 5% | 5%
Musculoskeletal system
Back pain | 6% | 8%
Arthralgia | 5% | 9%
Urogenital system
Urinary tract infection | 5% | 9%

The following adverse reactions occurred in 1 to < 5% of patients treated with FIRMAGON:

Body as a whole: Asthenia, fatigue, fever, night sweats
Digestive system: Nausea
Nervous system: Dizziness, headache, insomnia

The following adverse reactions, not already listed, occurred in ≥ 1% of patients treated in any study with FIRMAGON:

Reproductive System: Erectile dysfunction, testicular atrophy
Endocrine Disorders: Gynecomastia
General: Hyperhidrosis
Gastrointestinal: Diarrhea

Injection Site Reactions

The most frequently reported adverse reactions at the injection sites were pain (28%), erythema (17%), swelling (6%), induration (4%) and nodule (3%). These adverse reactions were mostly transient, of mild to moderate intensity, occurred primarily with the starting dose and led to few discontinuations (<1%). Grade 3 injection site reactions occurred in 2% or less of patients receiving FIRMAGON.

Hepatic Laboratory Abnormalities

Hepatic laboratory abnormalities were primarily Grade 1 or 2 and were generally reversible. Grade 3 hepatic laboratory abnormalities occurred in less than 1% of patients.

FIRMAGON Extension Study

The safety of FIRMAGON administered once every 28 days was evaluated further in an extension study (NCT00451958) in 385 patients who completed the above active-controlled trial. Of the 385 patients, 251 patients continued treatment with FIRMAGON and 135 patients crossed over treatment from leuprolide to FIRMAGON. The median treatment duration on the extension study was approximately 43 months (range 1 to 58 months). The most common adverse reactions reported in ≥10% of the patients were injection site reactions (e.g., pain, erythema, swelling, induration or inflammation), pyrexia, hot flush, weight loss or gain, fatigue, increases in serum levels of hepatic transaminases and GGT. One percent of patients had injection site infections including abscess. Hepatic laboratory abnormalities in the extension study included the following: Grade 1/2 elevations in hepatic transaminases occurred in 47% of patients and Grade 3 elevations occurred in 1% of patients.

6.2 Immunogenicity

As with all peptides, there is potential for immunogenicity. The detection of antibody formation is highly dependent on the sensitivity and specificity of the assay. Additionally, the observed incidence of antibody (including neutralizing antibody) positivity in an assay may be influenced by several factors including assay methodology, sample handling, timing of sample collection, concomitant medications, and underlying disease.

Anti-Degarelix Antibodies

Anti-degarelix antibody development has been observed in 10% of patients after treatment with FIRMAGON for 1 year. There is no indication that the efficacy or safety of FIRMAGON treatment is affected by antibody formation.

6.3 Postmarketing Experience

The following adverse reactions have been identified during post-approval use of FIRMAGON. Because these reactions are reported voluntarily from a population of uncertain size, it is not always possible to reliably estimate their frequency or establish a causal relationship to drug exposure.

Changes in bone density

Decreased bone density has been reported in the medical literature in men who have had orchiectomy or who have been treated with a GnRH agonist. It can be anticipated that long periods of medical castration in men will result in decreased bone density.

7 DRUG INTERACTIONS

No drug-drug interaction studies were conducted.

Degarelix is not a substrate for the human CYP450 system. Degarelix is not an inducer or inhibitor of the CYP450 system in vitro. Therefore, clinically significant CYP450 pharmacokinetic drug-drug interactions are unlikely.

8 USE IN SPECIFIC POPULATIONS

8.1 Pregnancy

Risk Summary

The safety and efficacy of FIRMAGON have not been established in women.

Based on findings in animal studies and mechanism of action, FIRMAGON can cause fetal harm and loss of pregnancy when administered to a pregnant woman [see Clinical Pharmacology (12.1)]. There are no human data on the use of FIRMAGON in pregnant women to inform the drug-associated risk. In animal developmental and reproductive toxicity studies in rats and rabbits, oral administration of degarelix during organogenesis caused embryo-fetal lethality and abortion as well as increased post-implantation loss and decreased the number of live fetuses in animals at doses less than the clinical loading dose based on body surface area (see Data). Advise pregnant patients and females of reproductive potential of the potential risk to the fetus.

Data

Animal Data

When degarelix was given to rabbits during early organogenesis at doses of 0.002 mg/kg/day (about 0.02% of the clinical loading dose based on body surface area), there was an increase in early post-implantation loss. Degarelix given to rabbits during mid and late organogenesis at doses of 0.006 mg/kg/day (about 0.05% of the clinical loading dose based on body surface area) caused embryo/fetal lethality and abortion. When degarelix was given to female rats during early organogenesis, at doses of 0.0045 mg/kg/day (about 0.036% of the clinical loading dose based on body surface area), there was an increase in early post-implantation loss. When degarelix was given to female rats during mid and late organogenesis, at doses of 0.045 mg/kg/day (about 0.36% of the clinical loading dose based on body surface area), there was an increase in the number of minor skeletal abnormalities and variants.

8.2 Lactation

The safety and efficacy of FIRMAGON have not been established in females. There are no data on the presence of degarelix in human milk, the effects on the breastfed child, or the effects on milk production. Because many drugs are present in human milk and because of the potential for serious adverse reactions in a breastfed child from degarelix, a decision should be made whether to discontinue nursing or discontinue the drug taking into account the importance of the drug to the mother.

8.3 Females and Males of Reproductive Potential

Infertility

Based on findings in animals and mechanism of action, degarelix may impair fertility in males and females of reproductive potential [see Nonclinical Toxicology (13.1)].

8.4 Pediatric Use

Safety and effectiveness in pediatric patients have not been established.

8.5 Geriatric Use

Of the total number of subjects in clinical studies of FIRMAGON, 82% were age 65 and over, while 42% were age 75 and over. No overall differences in safety or effectiveness were observed between these subjects and younger subjects, but greater sensitivity of some older individuals cannot be ruled out.

8.6 Renal Impairment

No pharmacokinetic studies in renally impaired patients have been conducted. At least 20-30% of a given dose of degarelix is excreted unchanged in the urine. A population pharmacokinetic analysis of data from the randomized study demonstrated that there is no significant effect of mild renal impairment [creatinine clearance (CrCL) 50-80 mL/min] on either the degarelix concentration or testosterone concentration. Data on patients with moderate or severe renal impairment is limited and therefore degarelix should be used with caution in patients with CrCL < 50 mL/min.

8.7 Hepatic Impairment

Patients with hepatic impairment were excluded from the randomized trial.

A single dose of 1 mg degarelix administered as an intravenous infusion over 1 hour was studied in 16 non-prostate cancer patients with either mild (Child Pugh A) or moderate (Child Pugh B) hepatic impairment. Compared to non-prostate cancer patients with normal liver function, the exposure of degarelix decreased by 10% and 18% in patients with mild and moderate hepatic impairment, respectively. Therefore, dose adjustment is not necessary in patients with mild or moderate hepatic impairment. However, since hepatic impairment can lower degarelix exposure, it is recommended that in patients with hepatic impairment testosterone concentrations should be monitored on a monthly basis until medical castration is achieved. Once medical castration is achieved, an every-other-month testosterone monitoring approach could be considered.

Patients with severe hepatic dysfunction have not been studied and caution is therefore warranted in this group.

10 OVERDOSAGE

There have been no reports of overdose with FIRMAGON. In the case of overdose, however, discontinue FIRMAGON, treat the patient symptomatically, and institute supportive measures.

11 DESCRIPTION

FIRMAGON is a sterile lyophilized powder for injection containing degarelix (as the acetate) and mannitol. Degarelix is a synthetic linear decapeptide amide containing seven unnatural amino acids, five of which are D-amino acids. The acetate salt of degarelix is a white to off-white amorphous powder of low density as obtained after lyophilization.

The chemical name of degarelix is D-Alaninamide, N-acetyl-3-(2-naphthalenyl)-D-alanyl-4-chloro-D-phenylalanyl-3-(3-pyridinyl)-D-alanyl-L-seryl-4-[[[(4S)-hexahydro-2,6-dioxo-4-pyrimidinyl]carbonyl]amino]-L phenylalanyl-4-[(aminocarbonyl)amino]-D-phenylalanyl-L-leucyl-N6–(1-methylethyl)-L-lysyl-L-prolyl. It has an empirical formula of C82H103N18O16Cl and a molecular weight of 1632.3 Da.

Degarelix acetate has the following structural formula:

FIRMAGON is available in two packaging configurations:

- Starting Dose: Two vial carton with each vial delivering 120 mg of degarelix (equivalent to the median value of 126 mg degarelix acetate). Each 120 mg dose contains 150 mg mannitol.
- Maintenance Dose: One-vial carton delivering 80 mg of degarelix (equivalent to the median value of 84 mg degarelix acetate). Each 80 mg dose contains 200 mg mannitol.

12 CLINICAL PHARMACOLOGY

12.1 Mechanism of Action

Degarelix is a GnRH receptor antagonist. It binds reversibly to the pituitary GnRH receptors, thereby reducing the release of gonadotropins and consequently testosterone.

12.2 Pharmacodynamics

A single dose of 240 mg FIRMAGON causes a decrease in the plasma concentrations of luteinizing hormone (LH) and follicle stimulating hormone (FSH), and subsequently testosterone.

FIRMAGON is effective in achieving and maintaining testosterone suppression below the castration level of 50 ng/dL.

Figure 1: Plasma Testosterone Levels from Day 0 to 364 for Degarelix 240 mg/80 mg (Median with Interquartile Ranges)

12.3 Pharmacokinetics

Absorption

FIRMAGON forms a depot upon subcutaneous administration, from which degarelix is released to the circulation. Following administration of FIRMAGON 240 mg at a product concentration of 40 mg/mL, the mean Cmax was 26.2 ng/mL (coefficient of variation, CV 83%) and the mean AUC was 1054 ng∙day/mL (CV 35%). Typically Cmax occurred within 2 days after subcutaneous administration. In prostate cancer patients at a product concentration of 40 mg/mL, the pharmacokinetics of degarelix were linear over a dose range of 120 to 240 mg. The pharmacokinetic behavior of the drug is strongly influenced by its concentration in the injection solution.

Distribution

The distribution volume of degarelix after intravenous (> 1 L/kg) or subcutaneous administration (> 1000L) indicates that degarelix is distributed throughout total body water. In vitro plasma protein binding of degarelix is estimated to be approximately 90%.

Metabolism

Degarelix is subject to peptide hydrolysis during the passage of the hepato-biliary system and is mainly excreted as peptide fragments in the feces. No quantitatively significant metabolites were detected in plasma samples after subcutaneous administration. In vitro studies have shown that degarelix is not a substrate, inducer or inhibitor of the CYP450 or p-glycoprotein transporter systems.

Excretion

Following subcutaneous administration of 240 mg FIRMAGON at a concentration of 40 mg/mL to prostate cancer patients, degarelix is eliminated in a biphasic fashion, with a median terminal half-life of approximately 53 days. The long half-life after subcutaneous administration is a consequence of a very slow release of degarelix from the FIRMAGON depot formed at the injection site(s). Approximately 20-30% of a given dose of degarelix was renally excreted, suggesting that approximately 70-80% is excreted via the hepato-biliary system in humans. Following subcutaneous administration of degarelix to prostate cancer patients the clearance is approximately 9 L/hr.

Effect of Age, Weight and Race

There was no effect of age, weight or race on the degarelix pharmacokinetic parameters or testosterone concentration.

13 NONCLINICAL TOXICOLOGY

13.1 Carcinogenesis, Mutagenesis, Impairment of Fertility

Degarelix was administered subcutaneously to rats every 2 weeks for 2 years at doses of 2, 10 and 25 mg/kg (about 9, 45 and 120% of the recommended human loading dose on a mg/m^2 basis). Long term treatment with degarelix at 25 mg/kg caused an increase in the combined incidence of benign hemangiomas plus malignant hemangiosarcomas in females.

Degarelix was administered subcutaneously to mice every 2 weeks for 2 years at doses of 2, 10 and 50 mg/kg (about 5, 22 and 120% of the recommended human loading dose (240 mg) on a mg/m^2 basis). There was no statistically significant increase in tumor incidence associated with this treatment.

Degarelix did not cause genetic damage in standard in vitro assays (bacterial mutation, human lymphocyte chromosome aberration) nor in in vivo rodent bone marrow micronucleus tests.

Single degarelix doses of ≥ 1 mg/kg (about 5% of the clinical loading dose on a mg/m^2 basis) caused reversible infertility in male rats. Single doses of ≥ 0.1 mg/kg (about 0.5% of the clinical loading dose on a mg/m^2 basis) caused a decrease in fertility in female rats.

14 CLINICAL STUDIES

The safety and efficacy of FIRMAGON were evaluated in an open-label, multi-center, randomized, parallel-group study (NCT00295750) in patients with prostate cancer. A total of 620 patients were randomized to receive one of two FIRMAGON dosing regimens or leuprolide for one year:

a. FIRMAGON at a starting dose of 240 mg (40 mg/mL) followed by monthly doses of 80 mg (20 mg/mL) subcutaneously,
b. leuprolide 7.5 mg intramuscularly monthly.
c. FIRMAGON at a starting dose of 240 mg (40 mg/mL) followed by monthly doses of 160 mg (40 mg/mL) subcutaneously.

FIRMAGON is not approved for use with monthly doses of 160 mg (40 mg/mL) subcutaneously.

Serum levels of testosterone were measured at screening, on Day 0, 1, 3, 7, 14, and 28 in the first month, and then monthly until the end of the study.

The clinical trial population (n=610) across all treatment arms had an overall median age of approximately 73 (range 50 to 98). The ethnic/racial distribution was 84% white, 6% black and 10% others. Disease stage was distributed approximately as follows: 20% metastatic, 29% locally advanced (T3/T4 Nx M0 or N1 M0), 31% localized (T1 or T2 N0 M0) and 20% classified as other (including patients whose disease metastatic status could not be determined definitively - or patients with PSA relapse after primary curative therapy). In addition, the median testosterone baseline value across treatment arms was approximately 400 ng/dL.

The primary objective was to demonstrate that FIRMAGON is effective achieving and maintaining testosterone suppression to castration levels (T ≤ 50 ng/dL) during 12 months of treatment. The results are shown in Table 3.

Table 3: Medical Castration Rates (Testosterone ≤ 50 ng/dL) from Day 28 to Day 364
 | FIRMAGON 240/80 mg N=207 | Leuprolide 7.5 mg N=201
No. of Responders | 202 | 194
Castration Rate (95% CIs) [Kaplan Meier estimates within group] | 97.2% (93.5; 98.8) | 96.4% (92.5; 98.2)

Percentage changes in testosterone from baseline to Day 28 (median with interquartile ranges) are shown in Figure 2 and the percentages of patients who attained the medical castration of testosterone ≤ 50 ng/dL are summarized in Table 4.

Figure 2: Percentage Change in Testosterone from Baseline by Treatment Group until Day 28 (Median with Interquartile Ranges)

Table 4: Percentage of Patients Attaining Testosterone ≤ 50 ng/dL within the First 28 Days
 | FIRMAGON 240/80 mg N=207 | Leuprolide 7.5 mg N=201
Day 1 | 52% | 0%
Day 3 | 96% | 0%
Day 7 | 99% | 1%
Day 14 | 99% | 18%
Day 28 | 100% | 100%

In the clinical trial, PSA levels were monitored as a secondary endpoint. PSA levels were lowered by 64% two weeks after administration of FIRMAGON, 85% after one month, 95% after three months, and remained suppressed throughout the one year of treatment. These PSA results should be interpreted with caution because of the heterogeneity of the patient population studied. No evidence has shown that the rapidity of PSA decline is related to a clinical benefit.

16 HOW SUPPLIED/STORAGE AND HANDLING

FIRMAGON is available as:

- NDC 55566-8403-1, Starting dose – One carton contains:
  Two single-dose vials each delivering 120 mg of degarelix in a white to off-white lyophilized powder for injection
  Two prefilled syringes each containing 3 mL of Sterile Water for Injection, USP
  Two vial adapters
  Two administration needles
- NDC 55566-8303-1, Maintenance dose – One carton contains:
  One single-dose vial delivering 80 mg of degarelix in a white to off-white lyophilized powder for injection
  One prefilled syringe containing 4.2 mL of Sterile Water for Injection, USP
  One vial adapter
  One administration needle

STORAGE AND HANDLING

Store at 20°C to 25°C (68°F to 77°F); excursions permitted to 15°C to 30°C (59°F to 86°F). [see USP Controlled Room Temperature].

17 PATIENT COUNSELING INFORMATION

Advise the patient to read the FDA-approved patient labeling (Patient Information).

Hypersensitivity

- Inform patients that if they have experienced severe hypersensitivity with degarelix or to any of the product components, FIRMAGON is contraindicated [see Contraindications (4)]. Instruct patients to immediately report signs of a severe hypersensitivity reaction [see Warnings and Precautions (5.1)].

QT Interval Prolongation

- Advise patients that androgen deprivation therapy treatment with FIRMAGON may prolong the QT interval. Inform patients of the signs and symptoms of QT prolongation. Advise patients to contact their healthcare provider immediately for signs or symptoms of QT prolongation [see Warnings and Precautions (5.2)].

Androgen Deprivation

- Inform patients about adverese reactions related to androgen deprivation therapy with FIRMAGON, including hot flashes, flushing of the skin, increased weight, decreased sex drive, and difficulties with erectile function [see Adverse Reactions (6.1)].

Injection Site Reactions

- Inform patients that FIRMAGON may cause redness, swelling, and itching at the injection site. Advise patients that these adverse reactions are usually mild, self limiting, and decrease within three days [see Adverse Reactions (6.1)].

Infertility

- Inform patients that FIRMAGON may cause infertility [see Use in Specific Populations (8.3)].

MANUFACTURED FOR:

FERRING PHARMACEUTICALS INC., PARSIPPANY, NJ 07054
Manufactured in Germany

02/2020

Patient Information

FIRMAGON (FIRM-uh-gahn)
(degarelix for injection)

What is FIRMAGON?

FIRMAGON is a prescription medicine used in the treatment of advanced prostate cancer.
It is not known if FIRMAGON is safe or effective in children.

Who should not receive FIRMAGON?

Do not receive FIRMAGON if you are allergic to degarelix or any ingredient in FIRMAGON. See the end of this leaflet for a complete list of ingredients in FIRMAGON.

Talk to your healthcare provider before receiving FIRMAGON if you have any of these conditions.

Before receiving FIRMAGON, tell your healthcare provider about all your medical conditions, including if you:

- have any heart problems including a condition called long QT syndrome.
- have problems with blood levels such as sodium, potassium, calcium, and magnesium
- have kidney or liver problems
- are pregnant or plan to become pregnant. FIRMAGON can cause harm to your unborn baby and loss of pregnancy (miscarriage)
- are breastfeeding or plan to breastfeed. It is not known if FIRMAGON passes into your breast milk. You and your healthcare provider should decide if you will receive FIRMAGON or breastfeed. You should not do both.

Tell your healthcare provider about all the medicines you take, including prescription and over-the-counter medicines, vitamins, and herbal supplements.

Know the medicines you take. Keep a list of them and show it to your healthcare provider and pharmacist when you get a new medicine.

How will I receive FIRMAGON?

You will receive an injection of FIRMAGON from your healthcare provider.

- The injection site will always be in the stomach (abdominal area). The injection site will change within the stomach area each time you receive a dose of FIRMAGON.
- Two injections are given as a first dose. The following monthly doses are one injection.
- Do not rub or scratch the injection site. Make sure your injection site is free of any pressure from belts, waistbands or other types of clothing.
- Always set up an appointment for your next injection.

What are the possible side effects of FIRMAGON?

FIRMAGON can cause serious side effects, including:

- Serious allergic reactions. Get medical help right away if you get any of these symptoms:

- trouble breathing or wheezing
- severe itching

- swelling of your face, lips, mouth, or tongue

- Disorder of the heart's electrical activity. Your healthcare provider may do tests during treatment with FIRMAGON to check your heart for a condition called long QT syndrome.

The common side effects of FIRMAGON include:

- injection site pain, redness, and swelling
- hot flashes

- weight gain
- increase in some liver enzymes

Other side effects include decreased sex drive and erectile function problems.

Tell your healthcare provider if you have any side effect that bothers you or that does not go away.

These are not all the possible side effects.

Call your healthcare provider for medical advice about side effects. You may report side effects to FDA at 1-800-FDA-1088.

General information about the safe and effective use of FIRMAGON.

Medicines are sometimes prescribed for conditions that are not mentioned in a Patient Information leaflet. Do not use FIRMAGON for a condition for which it was not prescribed. Do not give FIRMAGON to other people, even if they have the same symptoms that you have. It may harm them.

You can ask your pharmacist or healthcare provider for information about FIRMAGON that is written for health professionals.

What are the ingredients in FIRMAGON?

Active ingredient: degarelix (as acetate)

Inactive ingredient: mannitol

MANUFACTURED FOR:

FERRING PHARMACEUTICALS INC., PARSIPPANY, NJ 07054
Manufactured in Germany

For more information, go to www.FIRMAGON.com or call 1-888-337-7464.

This Patient Information has been approved by the U.S. Food and Drug Administration.

02/2020

PRINCIPAL DISPLAY PANEL - 240 mg Kit Carton

NDC 55566-8403-1

FERRING
PHARMACEUTICALS

FIRMAGON® 240 mg*
(degarelix for injection)

*240 mg dose administered from
two vials each containing 120 mg

For single use subcutaneous injection only
Discard unused portion

Kit contents:
2 vials each with 120 mg powder for injection
2 syringes with Sterile Water for Injection, USP
for reconstitution/administration
2 vial adapters
2 administration needles

Starting Dose
Rx only

PRINCIPAL DISPLAY PANEL - 80 mg Kit Carton

NDC 55566-8303-1

FERRING
PHARMACEUTICALS

FIRMAGON® 80 mg
(degarelix for injection)

For single use subcutaneous injection only
Discard unused portion

Kit contents:
1 vial with 80 mg powder for injection
1 syringe with Sterile Water for Injection, USP
for reconstitution/administration
1 vial adapter
1 administration needle

Maintenance Dose (28 Days)
Rx only